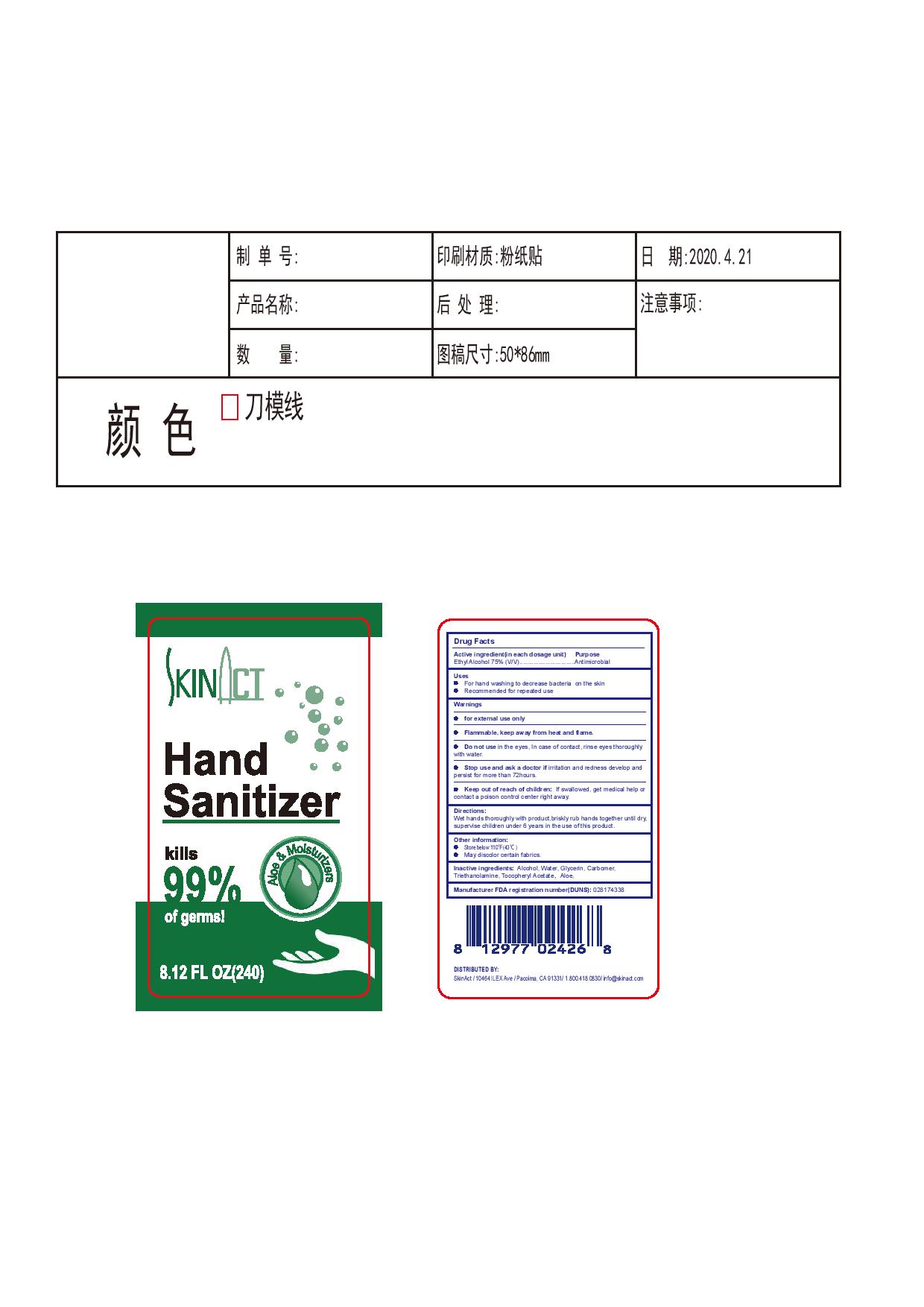 DRUG LABEL: Skinact
NDC: 78160-002 | Form: GEL
Manufacturer: Skinact
Category: otc | Type: HUMAN OTC DRUG LABEL
Date: 20200624

ACTIVE INGREDIENTS: ALCOHOL 75 mL/100 mL
INACTIVE INGREDIENTS: TROLAMINE; CARBOMER HOMOPOLYMER, UNSPECIFIED TYPE; GLYCERIN; WATER; ALPHA-TOCOPHEROL ACETATE; ALOE

Skinact Instant Hand Sanitizer Gel

Active Ingredient(s)

Ethyl Alcohol 75% v/v.

Purpose

Antimicrobial

Use

- For handwashing to decrease bacteria on the skin
- Recommended for repeated use

Warnings

For external use only. Flammable. Keep away from heat or flame

Do not use

in the eyses. In case of contact, rinse eyes thorooughly with water

When using this product keep out of eyes, ears, and mouth. In case of contact with eyes, rinse eyes thoroughly with water.
Stop use and ask a doctor if irritation or rash occurs. These may be signs of a serious condition.
Keep out of reach of children. If swallowed, get medical help or contact a Poison Control Center right away.

Stop use and ask a doctor if irritation or redness develop and persist for more than 72 hours

Keep out of reach of children. If swallowed, get medical help or contact a Poison Control Center right away.

Directions

Wet hands thorooughly with product, briskly rub hands together until dry, supervise children under 6 years in the use of this product.

Other information

- Store below 110F (43C)
- May discolor certain fabrics

Inactive ingredients

Water, Glycerin, Carbomer, Triethanolamine, Tocopheryl Acetate,Aloe.